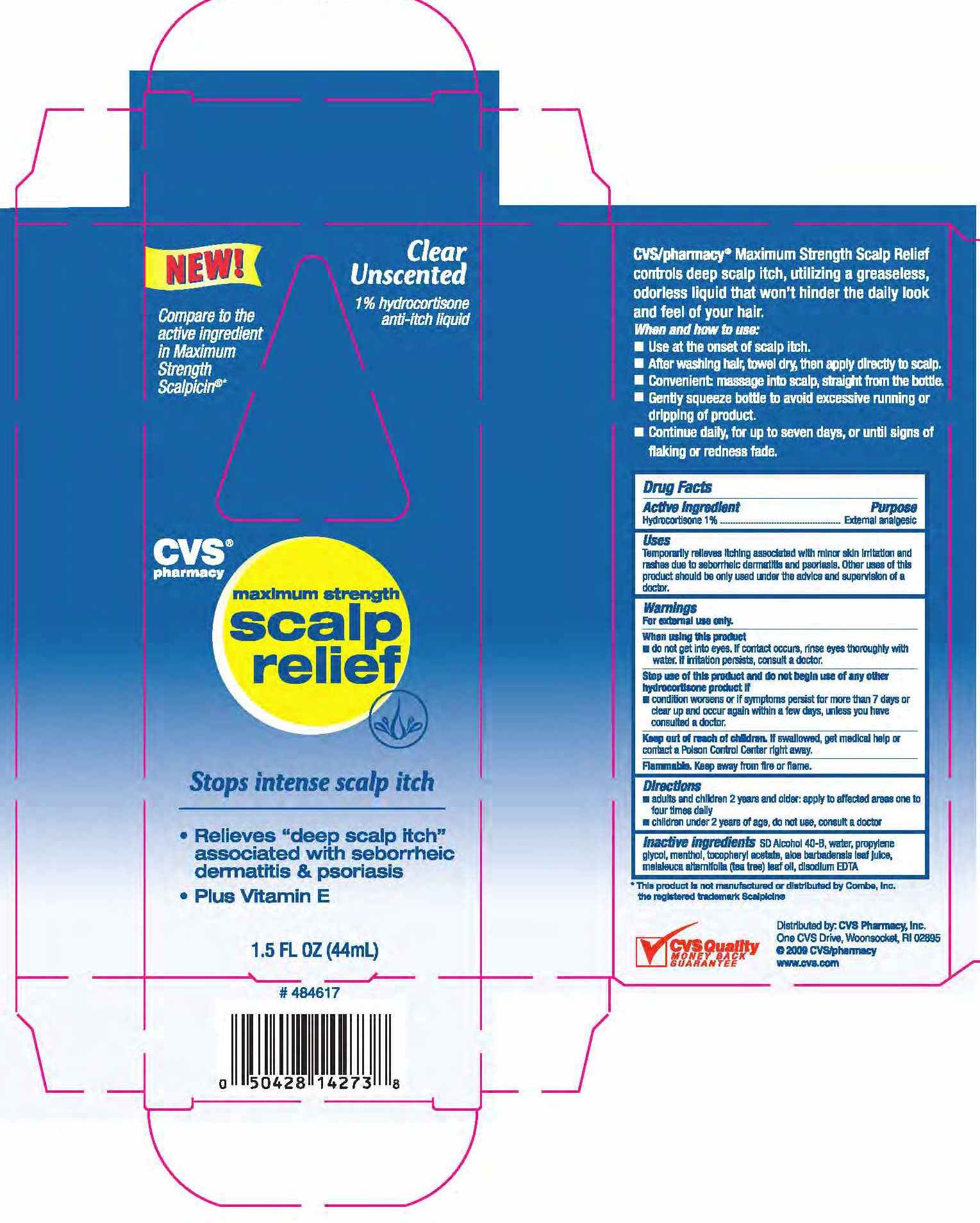 DRUG LABEL: HYDROCORTISONE 
NDC: 59779-318 | Form: LIQUID
Manufacturer: CVS Pharmacy
Category: otc | Type: HUMAN OTC DRUG LABEL
Date: 20100716

ACTIVE INGREDIENTS: HYDROCORTISONE 10 mg/1 mL
INACTIVE INGREDIENTS: WATER; ALCOHOL; MENTHOL; TEA TREE OIL; PROPYLENE GLYCOL; ALPHA-TOCOPHEROL ACETATE; EDETATE DISODIUM; ALOE VERA LEAF

drug facts

Active ingredient Purpose
Hydrocortisone 1%...................................External analgesic

Active ingredient Purpose
Hydrocortisone 1%...................................External analgesic
Uses Temporarily relieves itching associated with minor skin
irritation and rashes due to saborrheic dermatitis and psoriasis.
Other uses of this product should be only used under the advice
and supervision of a doctor.

Keep out of reach of children. If swallowed, get medical help
or contact a Poison Control Center right away.

Directions

- adults and children 2 years and older: apply to affected areas one to four times daily

- children under 2 years of age, do not use, consult a doctor

Warnings
For external use only.
When using this product
- do not get into eyes. If contact occurs, rinse eyes thoroughly with water. If irritation persists, consult a doctor.
Stop use of this product and do not begin use of any other hydrocortisone product if
- condition worsens or if symptoms persist for more than 7 days or clear up and occur again within a few days, unless you have consulted a doctor.
Keep out of reach of children. If swallowed, get medical
help or contact a Poison Control Center right away.
Flammable, Keep away from fire or flame.

Directions
- adults and children 2 years and older: apply to affected areas one to four times daily
- children under 2 years of age, do not use, consult a doctor

INACTIVE INGREDIENT

Inactive Ingredients SD Alcohol 40-B, water, propylene glycol, menthol, tocopheryl acetate,
aloe barbadensis leaf juice, meialeuce alternilolia (tea tree) leaf oil, disodium EDTA